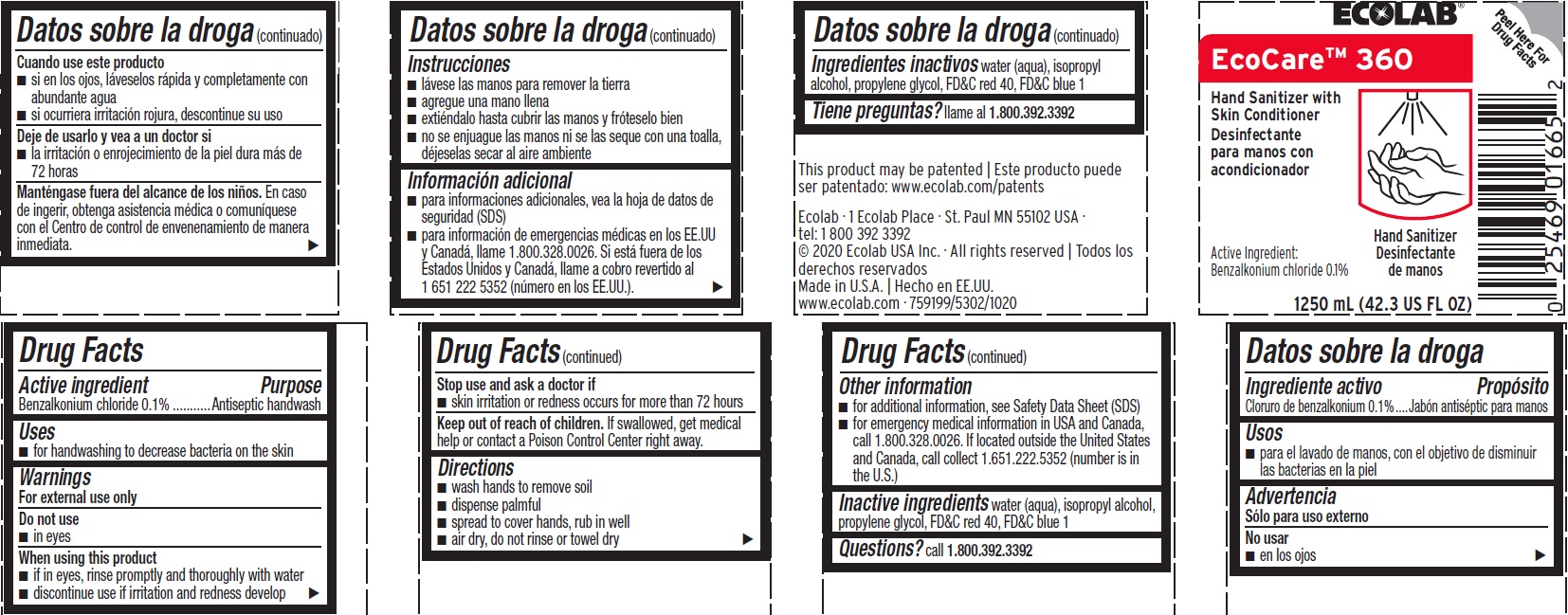 DRUG LABEL: EcoCare 360
NDC: 47593-275 | Form: SOLUTION
Manufacturer: Ecolab Inc.
Category: otc | Type: HUMAN OTC DRUG LABEL
Date: 20240313

ACTIVE INGREDIENTS: BENZALKONIUM CHLORIDE 0.1 mg/100 mL
INACTIVE INGREDIENTS: ISOPROPYL ALCOHOL; WATER; PROPYLENE GLYCOL; FD&C RED NO. 40; FD&C BLUE NO. 1

Drug Facts

Active ingredient

Benzalkonium chloride, 0.1%

Purpose

Antiseptic handwash

Uses

- for handwashing to decrease bacteria on the skin

Warnings

For external use only

Do not use

- In eyes

When using this product

- if in eyes, rinse promptly and thoroughly with water
- discontinue use if irritation and redness develop

Stop use and ask a doctor if

- skin irritation or redness persists for more than 72 hours

Keep out of reach of children. If swallowed, get medical help or contact a Poison Control Center right away.

Directions

- Wash hands to remove soil
- Dispense palmful
- Spread to cover hands, rub in well
- Air dry, do not rinse or towel dry

Other Information

- for additional information, see Safety Data Sheet (SDS)
- for emergency medical information in USA and Canada, call 1.800.328.0026. If located outside the United States and Canada, call collect 1.651.222.5352 (number is in the U.S.)

INACTIVE INGREDIENT

Inactive ingredients: water (aqua), isopropyl alcohol, propylene glycol, FD&C red 40, FD&C blue 1

Questions?

Call 1.800.392.3392

Principal Display Panel - Representative Label

ECOLAB

EcoCare 360

Hand Sanitizer with Skin Conditioner

Active Ingredient: Benzalkonium Chloride 0.1%

1250 mL (42.3 US Fl Oz

Ecolab · 1 Ecolab Place · St. Paul MN 55102 USA

tel: 1 800 392 3392

© 2020 Ecolab USA Inc. · All rights reserved | Todos los derechos reservados

Made in U.S.A. | Hecho en EE.UU.

www.ecolab.com · 759199/5302/1020